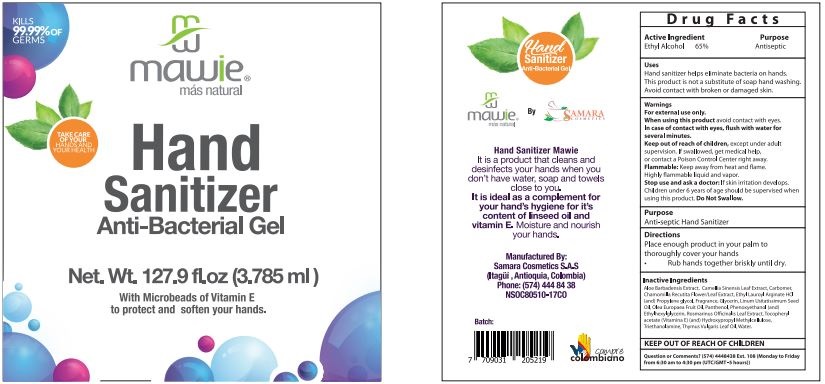 DRUG LABEL: Hand Sanitizer
NDC: 79894-007 | Form: GEL
Manufacturer: SAMARA COSMETICS S.A.S.
Category: otc | Type: HUMAN OTC DRUG LABEL
Date: 20200801

ACTIVE INGREDIENTS: ALCOHOL 68 mL/100 mL
INACTIVE INGREDIENTS: TROLAMINE 0.4 mL/100 mL; OLEA EUROPAEA FRUIT VOLATILE OIL 0.01 mL/100 mL; PANTHENOL 0.3 mL/100 mL; ALOE VERA LEAF 0.5 mL/100 mL; CHAMAEMELUM NOBILE FLOWER 0.3 mL/100 mL; THYMUS VULGARIS LEAF 0.1 mL/100 mL; .ALPHA.-TOCOPHEROL ACETATE 0.1 mL/100 mL; HYPROMELLOSES 0.1 mL/100 mL; PROPANEDIOL 0.2 mL/100 mL; PHENOXYETHANOL 0.72 mL/100 mL; FRAGRANCE CLEAN ORC0600327 0.3 mL/100 mL; ROSMARINUS OFFICINALIS FLOWER 0.3 mL/100 mL; LINUM USITATISSIMUM WHOLE 0.1 mL/100 mL; ETHYL LAUROYL ARGINATE HYDROCHLORIDE 0.1 mL/100 mL; ETHYLHEXYLGLYCERIN 0.07 mL/100 mL; CITRIC ACID MONOHYDRATE 0.1 mL/100 mL; WATER 29.79 mL/100 mL; POLYACRYLIC ACID (250000 MW) 0.1 mL/100 mL; GLYCERIN 0.5 mL/100 mL; CAMELLIA OIL 0.3 mL/100 mL

Hand Sanitizer

Uses

* Helps eliminate bacterias on the hand. This product is not a substitute of soap hand washing. Avoid contact with broken or damaged skin

Active Ingredient

Active Ingredient Purpose

- Ethyl Alcohol 65%...................................Antiseptic

Warnings

- For external use only-
- When using this product keep out o f eyes. In case of contact, flush with water several minutes.
- Keep out of reach of children except under adult supervision
- If swalow get medical help or contact a Poison Control Center right away.
- Flammable: Keep away from heat and flame.
- Stop use and ask Doctor: if skin irritation develops.
- Do not swalow
- Children under 6 years old should be supervised when using this product

Stop use and ask a doctor if

* Irritation develops

Keep out of reach of children. In case of incidental ingestion, see professional advice or contact a Poison Control Center inmediately.

Directions

- Place enough product in your palm to throughly cover your hands.
- Rub hands together briskly until dry

Inactive Ingredients

Water Carbomer, Triethanolamine, Olea Europaea Fruit Oil, Panthenol, Glycerin, Aloe Barbadensis Extract, Camellia Sinensis Leaf Extract, Chamomilla Recutita Flower/Leaf Extract, Rosmarinus Officinalis Leaf Extract, Thymus Vulgaris Leaf Oil, Linum Usitatissimum Seed Oil, Tocopheryl acetate (Vitamina E), Hydroxypropyl methylcellulose, Ethyl Lauroyl Arginate, Propylene Glycol, Fragrance, Phenoxyethanol, Ethylhexylglycerin, Citric Acid

Questions?

QUESTIONS OR COMMENTS: (574) 4448438 Ext 108 (Monday to Friday) 6:30 am to 4:30 pm (UTC/GMT 5 hours)

Uses

* Helps eliminate bacteria on the hand. This product is not a substitute of soap hand washing. Avoid contact with broken or damaged skin